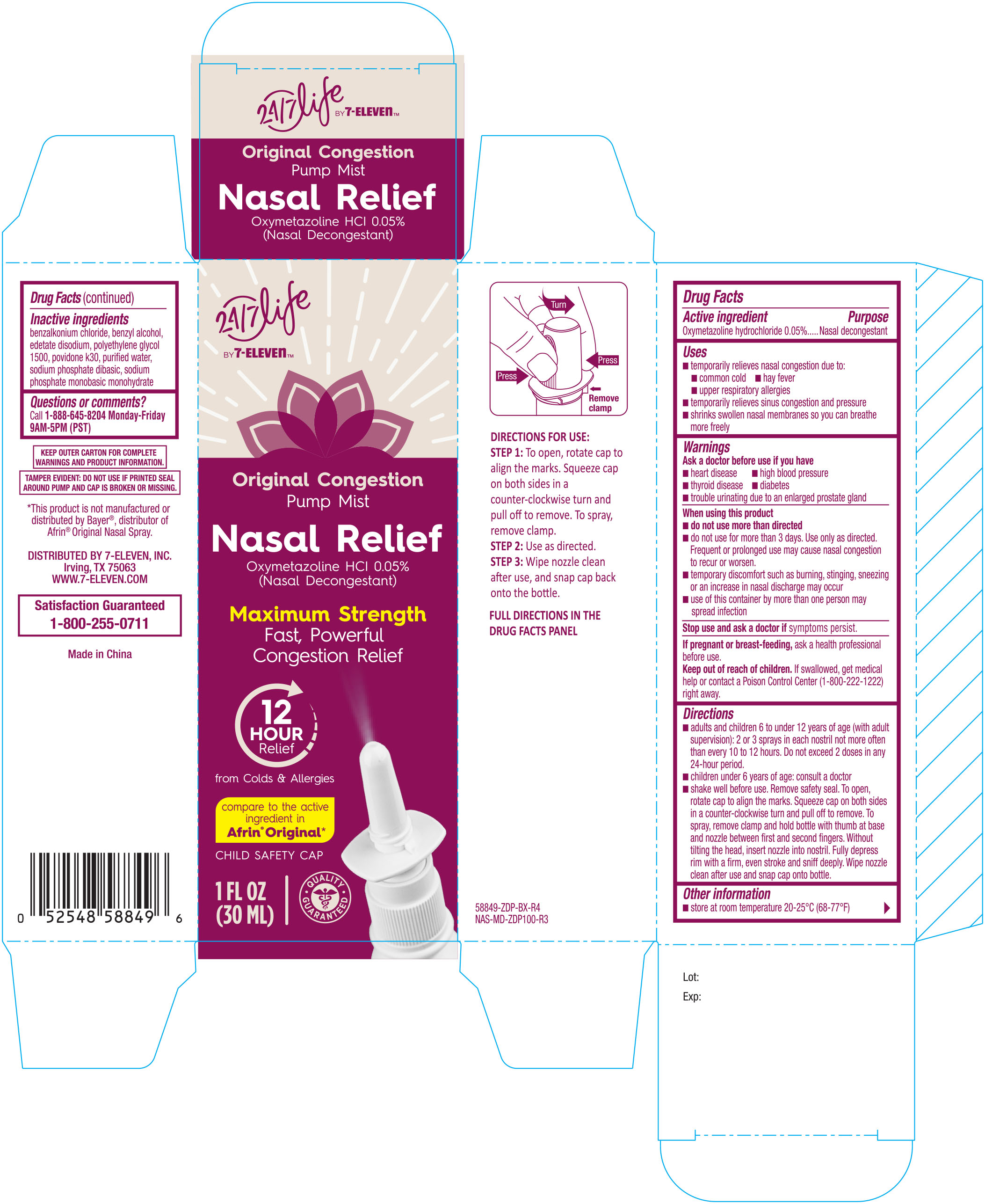 DRUG LABEL: 7 Select Original Nasal
NDC: 10202-849 | Form: SPRAY
Manufacturer: 7-ELEVEN, INC.
Category: otc | Type: HUMAN OTC DRUG LABEL
Date: 20191114

ACTIVE INGREDIENTS: OXYMETAZOLINE HYDROCHLORIDE 0.05 g/1 mL
INACTIVE INGREDIENTS: BENZYL ALCOHOL; SODIUM PHOSPHATE, DIBASIC, ANHYDROUS; EDETATE DISODIUM; WATER; POLYETHYLENE GLYCOL 1500; POVIDONE K30; SODIUM PHOSPHATE, MONOBASIC, MONOHYDRATE; BENZODODECINIUM CHLORIDE

7 Select Nasal Spray Original 1 oz (58849) 2019

Active ingredient Purpose

Oxymetazoline HCl 0.05%...........................Nasal decongestant

Uses

- temporarily relieves nasal congestion due to:
- common cold
- hay fever
- upper respiratory allergies
- temporarily relieves sinus congestion and pressure
- shrinks swollen nasal membranes so you can breathe more freely

Warnings

Ask a doctor before use if you have

- heart disease
- high blood pressure
- thyroid disease
- diabetes
- trouble urinating due to an enlarged prostate gland

When using this product

- do not use more than directed
- do not use for more than 3 days. Use only as directed. Frequent or prolonged use may cause nasal congestion to recur or worsen.
- temporary discomfort such as burning, stinging, sneezing or an increase in nasal discharge may occur
- use of this container by more than one person may spread infection

Stop use and ask a doctor if symptoms persist.

PREGNANCY OR BREAST FEEDING

If pregnant or breast-feeding, ask a health professional before use.

KEEP OUT OF REACH OF CHILDREN

Keep out of reach of childrean. If swallowed, get medical help or contact a Poison Control Center right away.

Directions

- adults and children 6 to under 12 years of age (with adult supervision): 2 or 3 sprays in each nostril not more than every 10 to 12 hours. Do not exceed 2 doeses in any 24-hour period.
- children under 6 years of age: ask a doctor. Shake well before use. To open, rotate cap to align the marks. Squeeze cap on both sides in a counter-clockwise turn and pull off to remove. To spray, remove clamp and hold bottle with thumb at base and nozzle between first and second fingers. Without tilting the head, insert nozzle into nostril. Fully depress rim with a firm, even stroke and sniff deeply. Wipe nozzle clean after use and snap cap back onto the bottle.

Other information

- store beween 20° to 25°C (68° to 77°F)
- retain carton for future reference on full labeling

Inactive ingredients

benzalkonium chloride, benzyl alcohol, edetate disodium, polyethylene glycol 1500, povidone k30, purified water, sodium phosphate dibasic, sodium phosphate monobasic

DOSAGE AND ADMINISTRATION

DISTRIBUTED BY 7-ELEVEN, INC.

Irving, TX 75063

WWW.7-ELEVEN.COM

Made in Korea